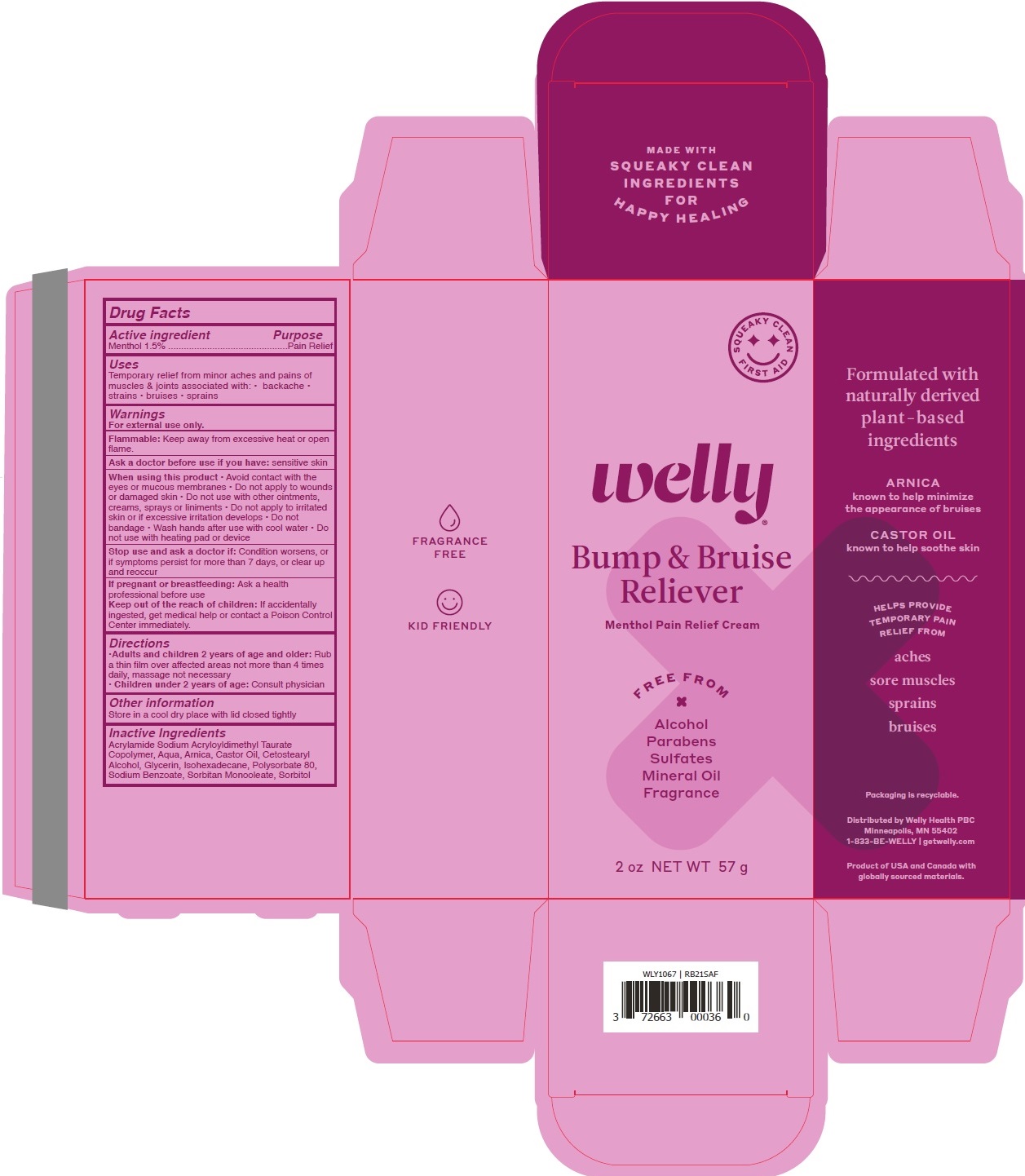 DRUG LABEL: Bump and Bruise Reliever
NDC: 72663-636 | Form: CREAM
Manufacturer: Welly Health PBC
Category: otc | Type: HUMAN OTC DRUG LABEL
Date: 20210225

ACTIVE INGREDIENTS: MENTHOL, UNSPECIFIED FORM 1.5 g/100 g
INACTIVE INGREDIENTS: SODIUM ACRYLOYLDIMETHYLTAURATE-ACRYLAMIDE COPOLYMER (1:1; 90000-150000 MPA.S); WATER; ARNICA MONTANA FLOWER; CASTOR OIL; CETOSTEARYL ALCOHOL; GLYCERIN; ISOHEXADECANE; POLYSORBATE 80; SODIUM BENZOATE; SORBITAN MONOOLEATE; SORBITOL

Bump and Bruise Reliever

Active ingredient

Menthol 1.5%

Purpose

Pain Relief

Uses

Temporary relief from minor aches and pains of muscles & joints associated with: • backache • strains • bruises • sprains

Warnings

For external use only.

Flammable: Keep away from excessive heat or open flame.

Ask a doctor before use if you have: sensitive skin

When using this product • Avoid contact with the eyes or mucous membranes • Do not apply to wounds or damaged skin • Do not use with

other ointments, creams, sprays or liniments • Do not apply to irritated skin or if excessive irritation develops • Do not bandage

• Wash hands after use with cool water • Do not use with heating pad or device

Stop use and ask a doctor if: Condition worsens, or if symptoms persist for more than 7 days, or clear up and reoccur

If pregnant or breastfeeding: Ask a health professional before use

KEEP OUT OF REACH OF CHILDREN

Keep out of the reach of children: If accidentally ingested, get medical help or contact a Poison Control Center immediately.

Directions

• Adults and children 2 years of age and older: Rub a thin film over affected areas not more than 4 times daily, massage not necessary

• Children under 2 years of age: Consult physician

Other information

Store in a cool dry place with lid closed tightly

Inactive Ingredients

Acrylamide Sodium Acryloyldimethyl Taurate Copolymer, Aqua, Arnica, Castor Oil, Cetostearyl Alcohol, Glycerin, Isohexadecane, Polysorbate 80,

Sodium Benzoate, Sorbitan Monooleate, Sorbitol

Menthol Pain Relief Cream

FREE FROM

x

Alcohol

Parabens

Sulfates

Mineral Oil

Fragrance

FRAGRANCE FREE

KID FRIENDLY

MADE WITH SQUEAKY CLEAN INGREDIENTS FOR HAPPY HEALING

SQUEAKY CLEAN FIRST AID

Formulated with naturally derived plant-based ingredients

ARNICA known to help minimize the appearance of bruises

CASTOR OIL known to help soothe skin

HELPS PROVIDE TEMPORARY PAIN RELIEF FROM

aches

sore muscles

sprains

bruises

Packaging is recyclable.

Distributed by Welly Health PBC

Minneapolis, MN 55402

1-833-BE-WELLY | getwelly.com

Product of USA and Canada with globally sourced materials.